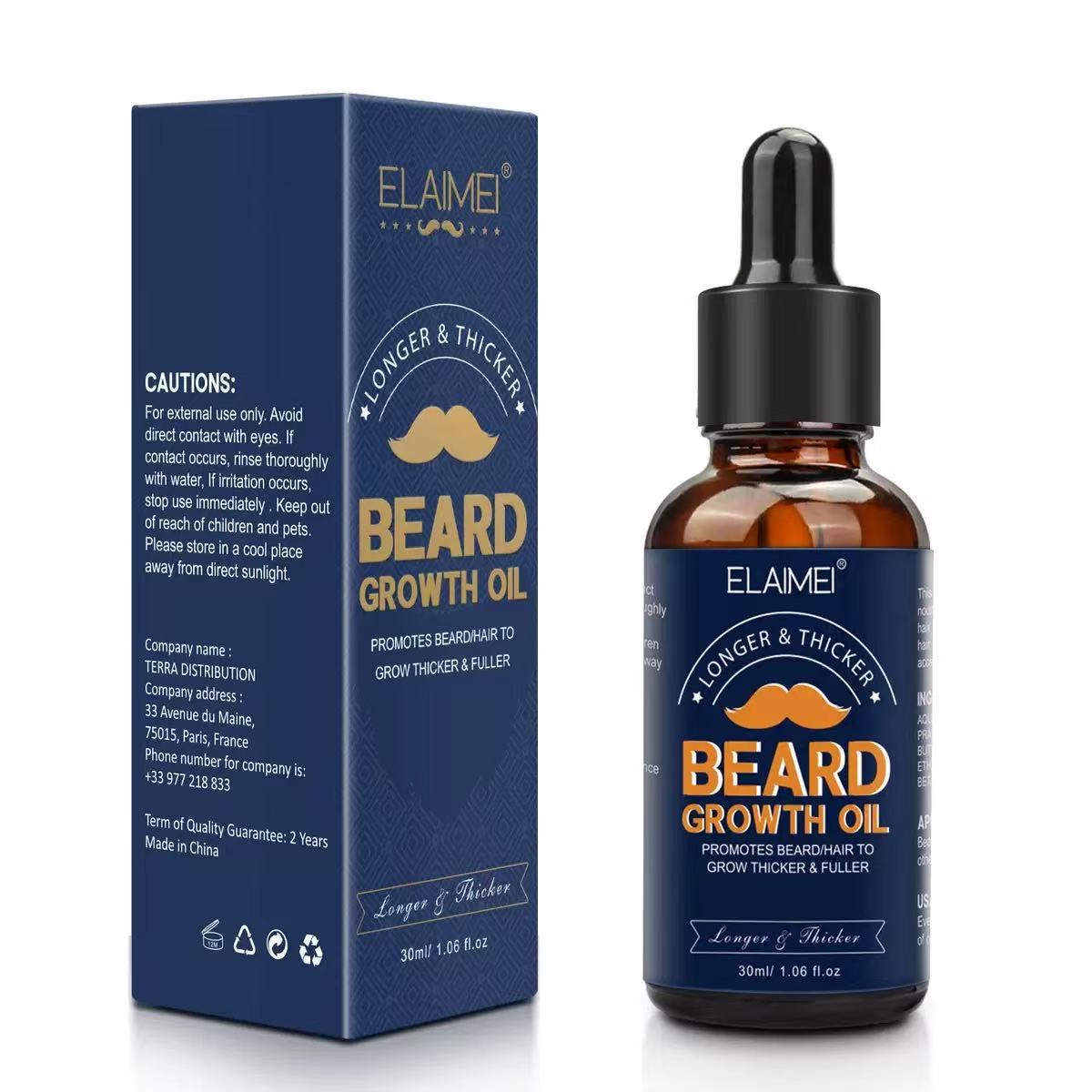 DRUG LABEL: Beard Growth Essence
NDC: 84854-001 | Form: SOLUTION
Manufacturer: Guangzhou Kanglixin Medical Biotechnology Co., Ltd.
Category: otc | Type: HUMAN OTC DRUG LABEL
Date: 20250810

ACTIVE INGREDIENTS: MYRISTOYL PENTAPEPTIDE-4 0.5 mg/1 g; BIOTINOYL TRIPEPTIDE-1 0.5 mg/1 g
INACTIVE INGREDIENTS: CAFFEINE; PANAX GINSENG ROOT; 1,3-BUTANEDIOL CYCLIC SULFITE; HYDROXYACETOPHENONE; 1,2-HEXANEDIOL; HYDROXYPROPYL .ALPHA.-CYCLODEXTRIN; HYALURONATE SODIUM; DEXPANTHENOL; EDETATE DISODIUM; POLYACRYLATE CROSSPOLYMER-6; HYDROLYZED ELASTIN

ACTIVE INGREDIENT

BIOTINOYL TRIPEPTIDE-1 0.05%

MYRISTOYL PENTAPEPTIDE-4 0.05%

INACTIVE INGREDIENT

WATER 84.28%

1,3-BUTANEDIOL CYCLIC SULFITE 10%

DEXPANTHENOL 1%

HYDROXYACETOPHENONE 0.5%

1,2-HEXANEDIOL 0.5%

POLYACRYLATE CROSSPOLYMER-6 0.25%

HYDROLYZED ELASTIN 0.2%

HYALURONATE SODIUM 0.15%

CAFFEINE 1%

Cyclodextrin 1%

PANAX GINSENG ROOT 1%

EDETATE DISODIUM 0.02%

PURPOSE

Beard Growth

INSTRUCTIONS FOR USE

Apply 1 ml (few drops) directly onto the area where you want to grow beard.
Use fingertips to massage solution into skin/beard for 2-3 minutes.
Allow time for fully absorption, don't apply anything for a few hours.

WHEN USING

Do not apply on other parts of the body.
Avoid contact with the eyes. In case of accidental contact, rinse eyes with large amounts of cool clean water.
It takes time to grow beard.
For some men, you may need to use this product for at least 1 month before you see results.
The amount of beard growth is different for each person.
This product will not work for all men.

WARNINGS

For external use only.

For use by men only.

STOP USE

Skin irritation or redness occurs
You do not see beard regrowth in 4 months

STORAGE AND HANDLING

Store in a cool, dry place.
Keep out of direct sunlight.
Keep the cap on tightly when not in use.

KEEP OUT OF REACH OF CHILDREN

DOSAGE AND ADMINISTRATION

Apply 1 ML(few drops)directly on the beard area.Use fingertips to massage solution into skin/hair for 2-3 minutes or use a roller to roll 4-5 timesAllow time for hair to fully absorb, don't apply anything for a few hours.

INDICATIONS AND USAGE

Do not apply on other parts of the body
Avoid contact with the eyes. in case of accidental contact, rinse eyes with large amounts of cool tap water.

PACKAGE LABEL

Beard Growth Essence